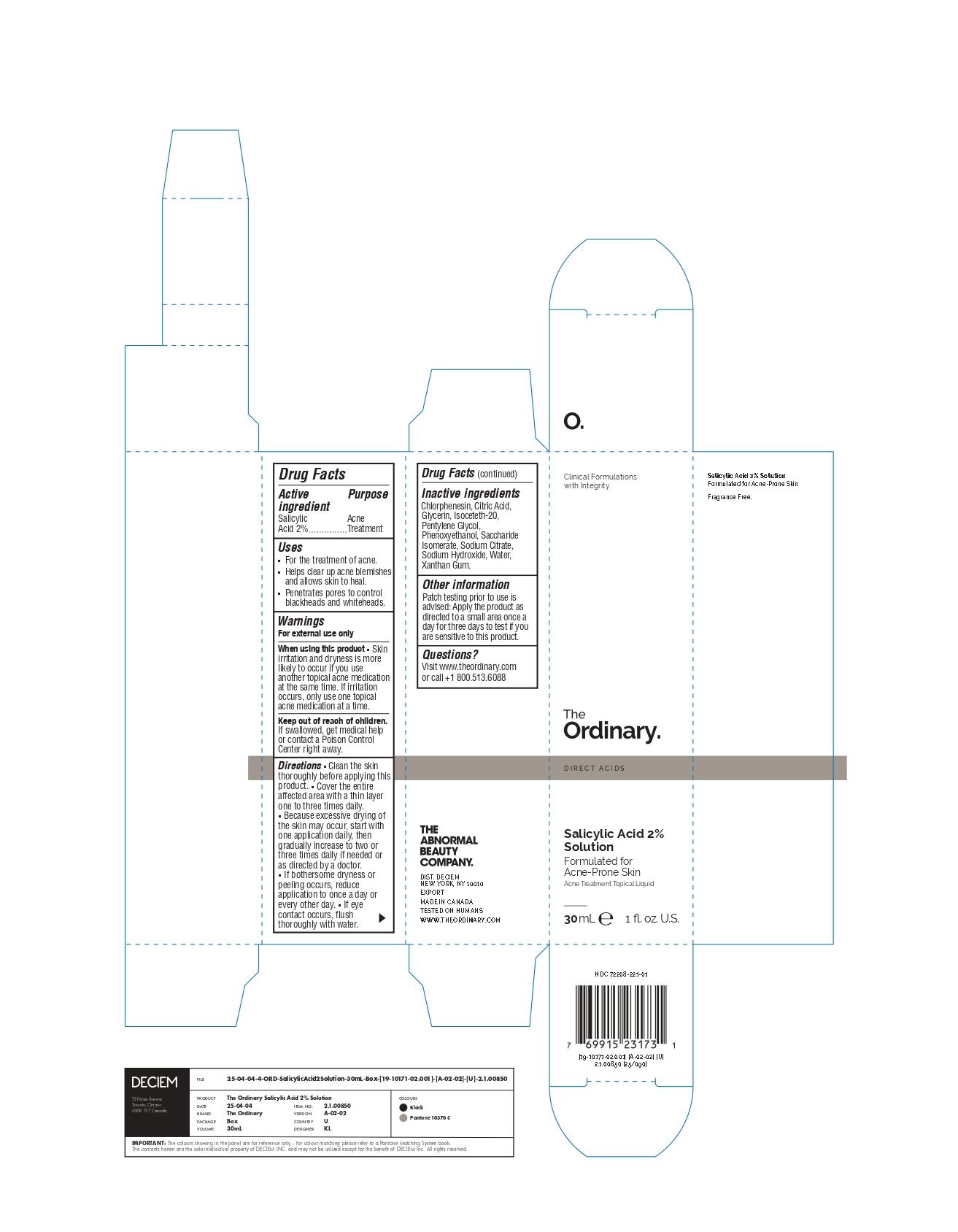 DRUG LABEL: Salicylic Acid 2% Solution
NDC: 72208-221 | Form: LOTION
Manufacturer: Deciem
Category: otc | Type: HUMAN OTC DRUG LABEL
Date: 20250909

ACTIVE INGREDIENTS: SALICYLIC ACID 20 mg/1 mL
INACTIVE INGREDIENTS: GLYCERIN; PENTYLENE GLYCOL; SODIUM HYDROXIDE; XANTHAN GUM; SACCHARIDE ISOMERATE; MONOSODIUM CITRATE; ANHYDROUS CITRIC ACID; ISOCETETH-20; PHENOXYETHANOL; WATER; CHLORPHENESIN

The Ordinary, Salicylic Acid 2% Solution